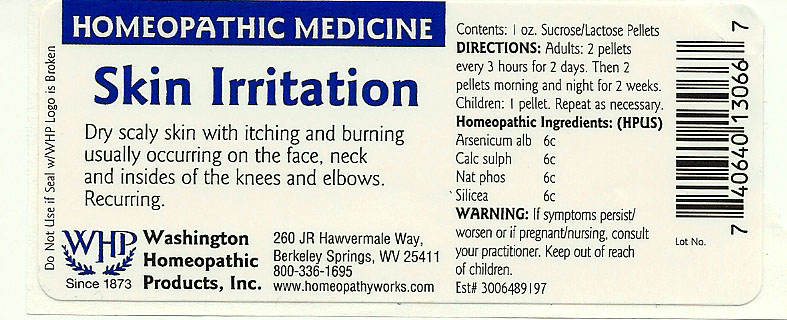 DRUG LABEL: Skin Irritation
NDC: 68428-016 | Form: PELLET
Manufacturer: Washington Homeopathic Products
Category: homeopathic | Type: HUMAN OTC DRUG LABEL
Date: 20151228

ACTIVE INGREDIENTS: ARSENIC TRIOXIDE 6 [hp_C]/28 g; CALCIUM SULFATE ANHYDROUS 6 [hp_C]/28 g; SODIUM PHOSPHATE, DIBASIC, HEPTAHYDRATE 6 [hp_C]/28 g; SILICON DIOXIDE 6 [hp_C]/28 g
INACTIVE INGREDIENTS: SUCROSE; LACTOSE

DRUG FACTS

ACTIVE INGREDIENTS

ARSENICUM ALB 6C

CALC SULPH 6C

NAT PHOS 6C

SILICEA 6C

USES

To relieve the symptoms of dry scaly skin with itching and burning usually occurring on the face, neck and insides of the knees and elbows.

KEEP OUT OF REACH OF CHILDREN

Keep this and all medicines out of reach of children.

INDICATIONS

ARSENICUM ALB Vomiting

CALC SULPH Boils

NAT PHOS Sour belching

SILICEA Formation of pus

STOP USE AND ASK DOCTOR

If symptoms persist/worsen or if pregnant/nursing, stop use and consult your practitioner.

DIRECTIONS

Adults 2 pellets every 3 hours for 2 days. Then 2 pellets morning and night for 2 weeks.

Children: 1 pellet. Repeat as necessary.

INACTIVE INGREDIENTS

Sucrose/Lactose

PRINCIPAL DISPLAY PANEL

Enter section text here